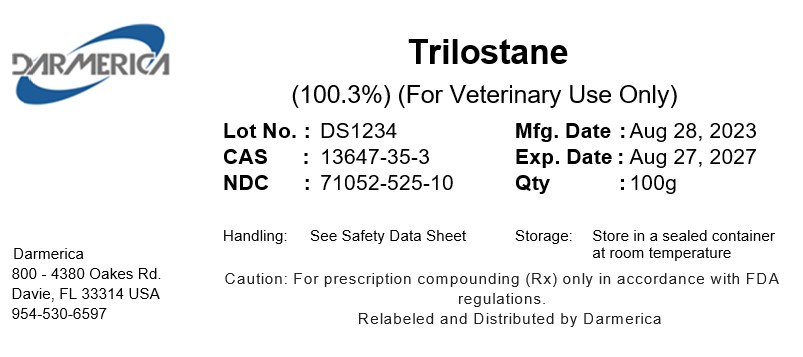 DRUG LABEL: Trilostane
NDC: 71052-525 | Form: POWDER
Manufacturer: DARMERICA, LLC
Category: other | Type: BULK INGREDIENT - ANIMAL DRUG
Date: 20250723

ACTIVE INGREDIENTS: TRILOSTANE 1 kg/1 kg

Trilostane